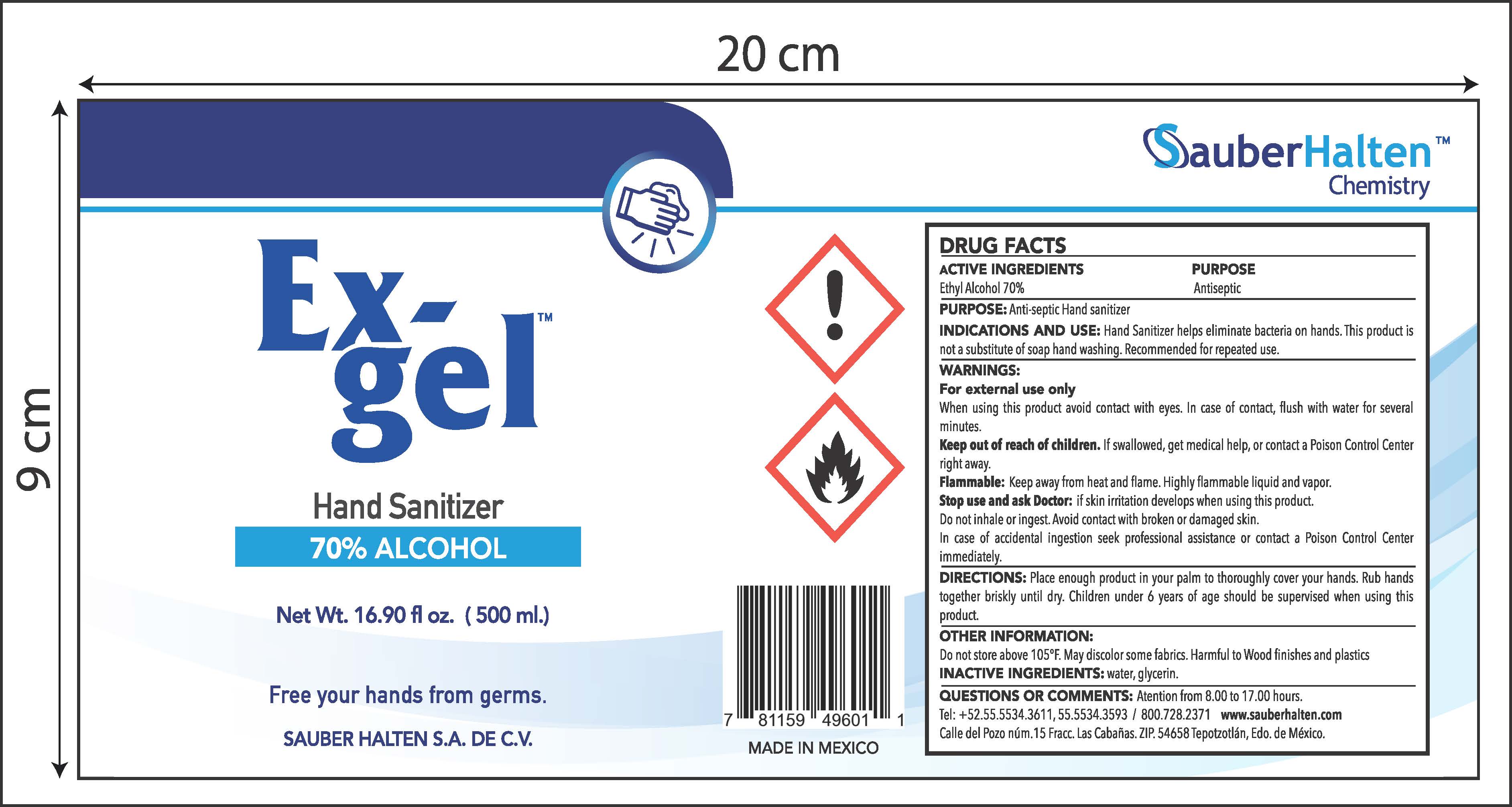 DRUG LABEL: Sauber Halten SA de CV
NDC: 76773-002 | Form: GEL
Manufacturer: Sauber Halten, S.A. de C.V.
Category: otc | Type: HUMAN OTC DRUG LABEL
Date: 20200512

ACTIVE INGREDIENTS: ALCOHOL 70 mg/1 mL
INACTIVE INGREDIENTS: GLYCERIN; WATER

Ex- Gel Hand Sanitizer

Active Ingredient

Active Ingredient Purpose

Ethyl Alcohol 70%............ Antibacterial

Uses

* Hand Sanitizer helps eliminate bacteria on hands. Antiseptic hand sanitizer

Warnings

- For external use only

When using this product avoid contact with eyes. In case of contact, flush with water for
several minutes.

- Keep out of reach of children. If swallowed, get medical help, or contact a Poison Control

Center right away.

- Flammable: Keep away from heat and flame. Highly flammable liquid and vapor.
- Stop use and ask Doctor: if skin irritation develops when using this product.
- Do not inhale or ingest. Avoid contact with broken or damaged skin.

In case of accidental ingestion seek professional assistance or contact a Poison Control
Center immediately.

Stop use and ask a doctor if

* Irritation develops while using this product

Keep out of reach of children. If swallowed, get medical help, or contact a Poison Control Center right away.

Directions

- Directions: Place enough product in your palm to thoroughly cover your hands. Rub hands together briskly until dry. Children under 6 years of age should be supervised when using this product.

Inactive Ingredients

Water, glycerin

Questions?

QUESTIONS OR COMMENTS: Atention from 8.00 to 17.00 hours.

Tel: +52.55.5534.3611, 55.5534.3593 / 800.728.2371 www.sauberhalten.com

Calle del Pozo núm.15 Fracc. Las Cabañas. ZIP. 54658 Tepotzotlán, Edo. de México.

Uses

* Hand Sanitizer helps eliminate bacteria on hands. Antiseptic hand sanitizer

Hand Sanitizer Gel

Antiseptic Hand Sanitizer Gel